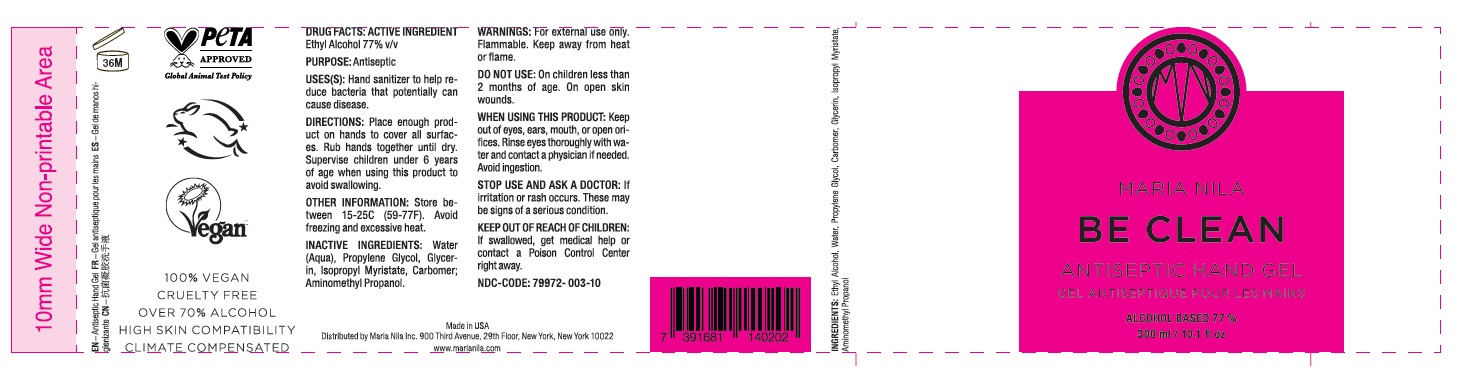 DRUG LABEL: BE CLEAN ANTISEPTIC HAND Gel
NDC: 79972-003 | Form: GEL
Manufacturer: Maria Nila Inc.
Category: otc | Type: HUMAN OTC DRUG LABEL
Date: 20200805

ACTIVE INGREDIENTS: ALCOHOL 77 mL/100 mL
INACTIVE INGREDIENTS: WATER; PROPYLENE GLYCOL; GLYCERIN; ISOPROPYL MYRISTATE; CARBOMER HOMOPOLYMER, UNSPECIFIED TYPE; AMINOMETHYLPROPANOL

MARIA NILA BE CLEAN ANTISEPTIC HAND GEL

ACTIVE INGREDIENT

Ethyl Alcohol 77% v/v

PURPOSE:

Antiseptic

INDICATIONS AND USAGE

USES(S): Hand sanitizer to help reduce bacteria that potentially can cause disease.

WARNINGS

WARNINGS: For external use only. Flammable. Keep away from heat or flame.

DO NOT USE: On children less than 2 months of age. On open skin wounds.

WHEN USING THIS PRODUCT: Keep out of eyes, ears, mouth, or open orifices. Rinse eyes thoroughly with water and contact a physician if needed. Avoid ingestion.

STOP USE AND ASK A DOCTOR: If irritation or rash occurs. These may be signs of a serious condition.

KEEP OUT OF REACH OF CHILDREN: If swallowed, get medical help or contact a Poison Control Center right away.

DOSAGE AND ADMINISTRATION

DIRECTIONS: Place enough product on hands to cover all surfaces. Rub hands together until dry. Supervise children under 6 years of age when using this product to avoid swallowing.

OTHER INFORMATION: Store between 15-25C (59-77F). Avoid freezing and excessive heat.

INACTIVE INGREDIENT

INACTIVE INGREDIENTS: Water (Aqua), Propylene Glycol, Glycerin, Isopropyl Myristate, Carbomer, Aminomethyl Propanol.

GEL MAINS ANTI-SEPTIQUE

ALCOHOL BASED 77%

100% VEGAN

CRUELTY FREE

HIGH SKIN COMPATIBILITY

CLIMATE COMPENSATED

Made in USA

Distributed by Maria Nila Inc. 900 Third Avenue, 29th Floor, New York, New York 10022

www.marianila.com